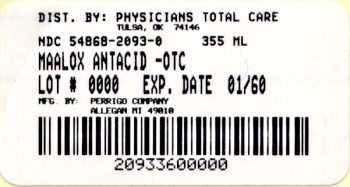 DRUG LABEL: Maalox Antacid
NDC: 54868-2093 | Form: LIQUID
Manufacturer: Physicians Total Care, Inc.
Category: otc | Type: HUMAN OTC DRUG LABEL
Date: 20120104

ACTIVE INGREDIENTS: ALUMINUM HYDROXIDE 200 mg/5 mL; MAGNESIUM HYDROXIDE 200 mg/5 mL; DIMETHICONE 20 mg/5 mL
INACTIVE INGREDIENTS: SILICON DIOXIDE; BUTYLPARABEN; CARBOXYMETHYLCELLULOSE SODIUM; HYPROMELLOSES; CELLULOSE, MICROCRYSTALLINE; PROPYLPARABEN; WATER; SACCHARIN SODIUM; SORBITOL

Active ingredient (in each 5 mL teaspoon)

Aluminum hydroxide (equiv. to dried gel, USP) 200 mg

Magnesium hydroxide 200 mg

Simethicone 20 mg

Purpose

Antacid

Antigas

Uses

for the relief of

- acid indigestion
- heartburn
- sour stomach
- upset stomach associated with these symptoms
- pressure and bloating commonly referred to as gas

Warnings

Ask a doctor before use if you have

- kidney disease
- a magnesium-restricted diet

Ask a doctor or pharmacist before use if you are

now taking a prescription drug. Antacids may interact with certain prescription drugs.

When using this product

do not exceed 16 teaspoonsful (80 mL) in a 24-hour period or use the maximum dosage for more than 2 weeks unless directed by a doctor

Directions

- shake well before using
- adults and children 12 years and older: take 2-4 tsp (10-20 mL) up to 4 times a day or as directed by a doctor
- children under 12: ask a doctor

Other information

- each teaspoon contains: calcium 25 mg and magnesium 85 mg
- store at 20°-25°C (68°-77°F)
- does not meet USP requirements for preservative effectiveness

Inactive ingredients

butylparaben, carboxymethylcellulose sodium, flavor, hypromellose, microcrystalline cellulose, propylparaben, purified water, saccharin sodium, simethicone emulsion, sorbitol

Questions or comments?

1-800-719-9260

Principal Display Panel

Regular Strength
Liquid Antacid
Antacid & Anti-Gas
Fast Relief of:
Heartburn
Acid Indigestion
Sour Stomach & Upset Stomach
Mint Flavor
Maalox Antacid 12 fl oz (355 mL)
NDC 54868-2093-0